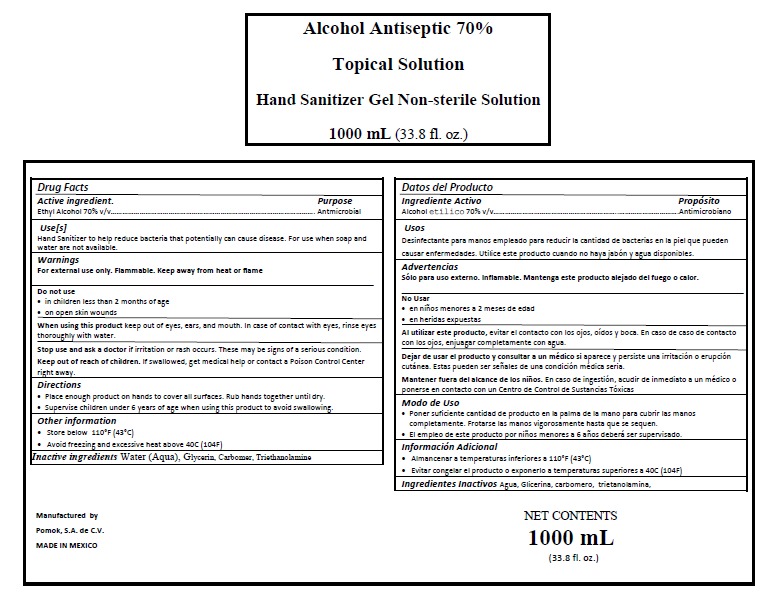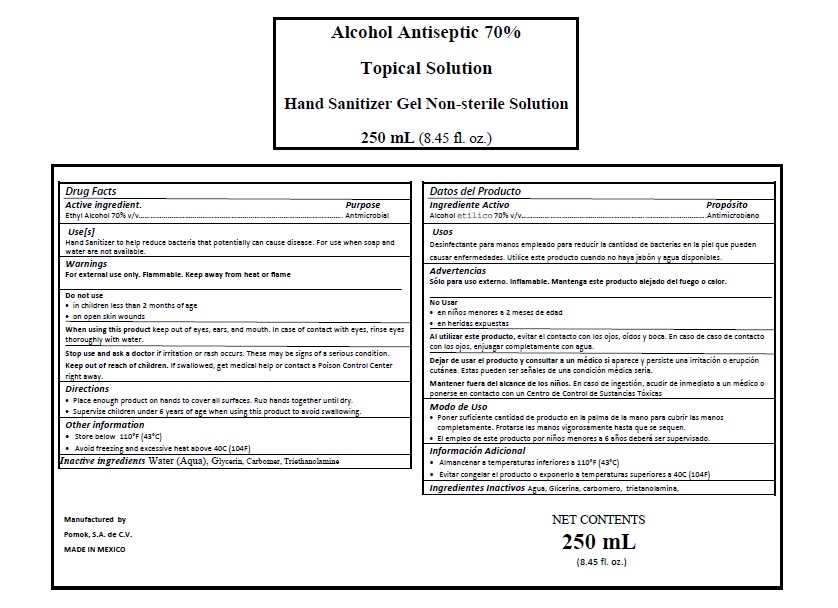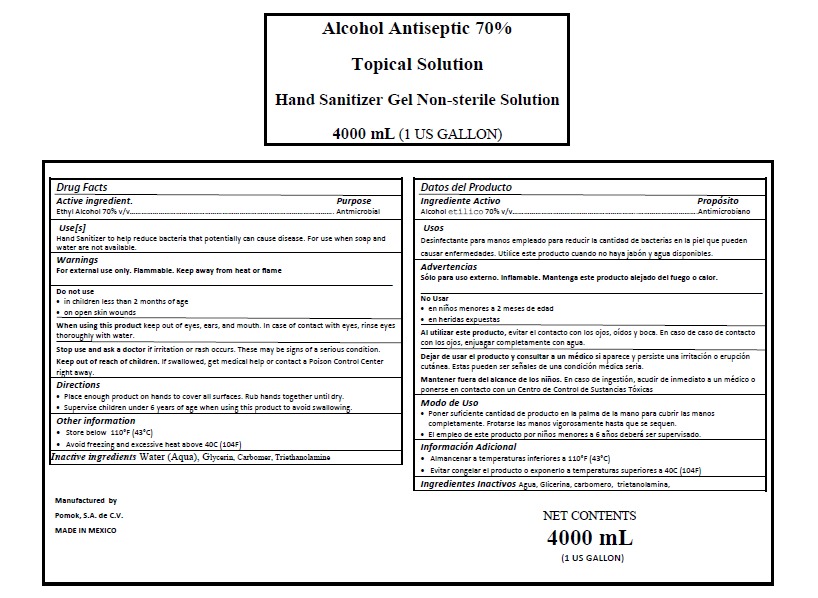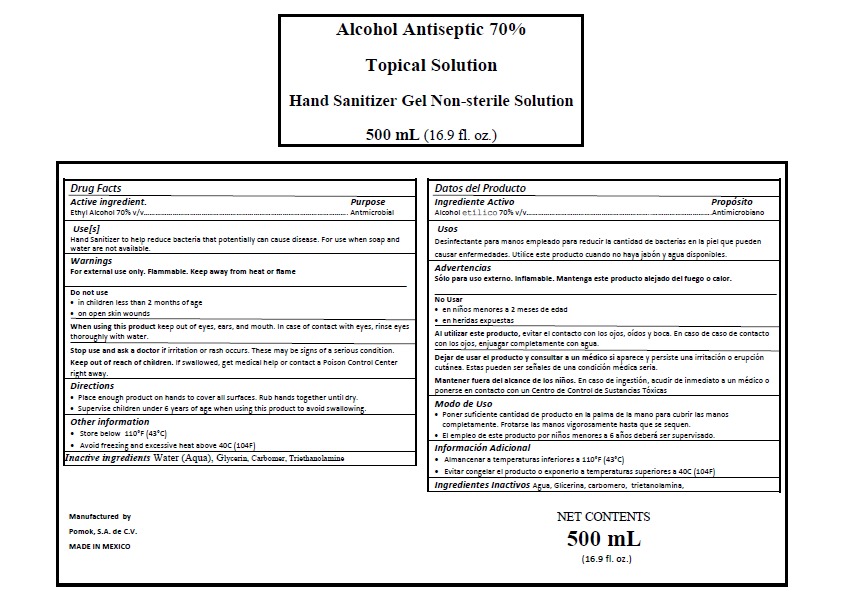 DRUG LABEL: HAND SANITIZER
NDC: 78354-0004 | Form: GEL
Manufacturer: Pomok, S.A. de C.V.
Category: otc | Type: HUMAN OTC DRUG LABEL
Date: 20200525

ACTIVE INGREDIENTS: ALCOHOL 0.7 mL/1 mL
INACTIVE INGREDIENTS: CARBOMER 940 0.002 mL/1 mL; GLYCERIN 0.0375 mL/1 mL; TRIETHANOLAMINE CAPROYL GLUTAMATE 0.002 mL/1 mL; WATER 0.2585 mL/1 mL

HAND SANITIZER 250 mL, 500 mL, 1000 mL, 4000 mL

DOSAGE AND ADMINISTRATION

Place enough product on hands to cover all surfaces. Rub hands together until dry.

INACTIVE INGREDIENTS

Inactive ingredients Water (Aqua), Glycerin, Carbomer, Triethanolamine

INDICATIONS AND USAGE

Place enough product on hands to cover all surfaces. Rub hands together until dry.

Keep out of reach of children. If swallowed, get medical help or contact a Poison Control Center right away

Supervise children under 6 years of age when using this product to avoid swallowing.

PURPOSE

PURPOSE ANTIMICROBIAL

Use[s]

Hand Sanitizer to help reduce bacteria that potentially can cause disease. For use when soap and water are not available.

WARNINGS AND PRECAUTIONS

Warnings

For external use only. Flammable. Keep away from heat or flame

Stop use and ask a doctor if irritation or rash occurs. These may be signs of a serious condition.

Keep out of reach of children. If swallowed, get medical help or contact a Poison Control Center right away.

Store below 110°F (43°C)

WARNINGS

For external use only. Flammable. Keep away from heat or

ACTIVE INGREDIENT

Active ingredient. Ethyl Alcohol 70%